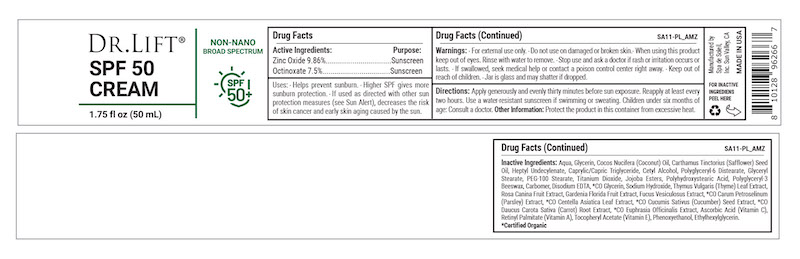 DRUG LABEL: Dr Lift SPF 50 Cream
NDC: 68062-9007 | Form: CREAM
Manufacturer: Spa de Soleil
Category: otc | Type: HUMAN OTC DRUG LABEL
Date: 20260121

ACTIVE INGREDIENTS: ZINC OXIDE 4.93 mg/50 mL; OCTINOXATE 3.75 mg/50 mL
INACTIVE INGREDIENTS: WATER; HEPTYL UNDECYLENATE; SAFFLOWER OIL; GLYCERIN; COCONUT OIL; CAPRYLIC/CAPRIC/LAURIC TRIGLYCERIDE

Moisturizer Sunscreen SPF 50

Active Ingredients

Zinc Oxide 9.86%

Octinoxate 7.5%

Purpose

Sunscreen

Warnings

Warnings When using this product

- keep out of the eye area
- rinse with water to remove
- stop use and ask a doctor if rash or irritation develops
- for external use onlyl
- keep out of reach of children

KEEP OUT OF REACH OF CHILDREN

Directions

Directions: Apply generously and evenly thirty minutes before sun exposure. Reapply at least every two hours. Use a water-resistant sunscreen if swimming or sweating.

Children under six months of age: Consult a doctor.

INDICATIONS AND USAGE

Apply generously and evenly thirty minutes before sun exposure. Reapply at least every two hours.

Inactive Ingredients

Inactive Ingredients: Aqua, Glycerin, Cocos Nucifera (Coconut) Oil, Carthamus Tinctorius (Safflower) Seed Oil, Heptyl Undecylenate, Caprylic/Capric Triglyceride, Cetyl Alcohol, Polyglyceryl-6 Distearate, Glyceryl Stearate, PEG-100 Stearate, Titanium Dioxide, Jojoba Esters, Polyhydroxystearic Acid, Polyglyceryl-3 Beeswax, Carbomer, Disodium EDTA, *CO Glycerin, Sodium Hydroxide, Thymus Vulgaris (Thyme) Leaf Extract, Rosa Canina Fruit Extract, Gardenia Florida Fruit Extract, Fucus Vesiculosus Extract, *CO Carum Petroselinum (Parsley) Extract, *CO Centella Asiatica Leaf Extract, *CO Cucumis Sativus (Cucumber) Seed Extract, *CO Daucus Carota Sativa (Carrot) Root Extract, *CO Euphrasia Officinalis Extract, Ascorbic Acid (Vitamin C), Retinyl Palmitate (Vitamin A), Tocopheryl Acetate (Vitamin E), Phenoxyethanol, Ethylhexylglycerin.

*Certified Organic